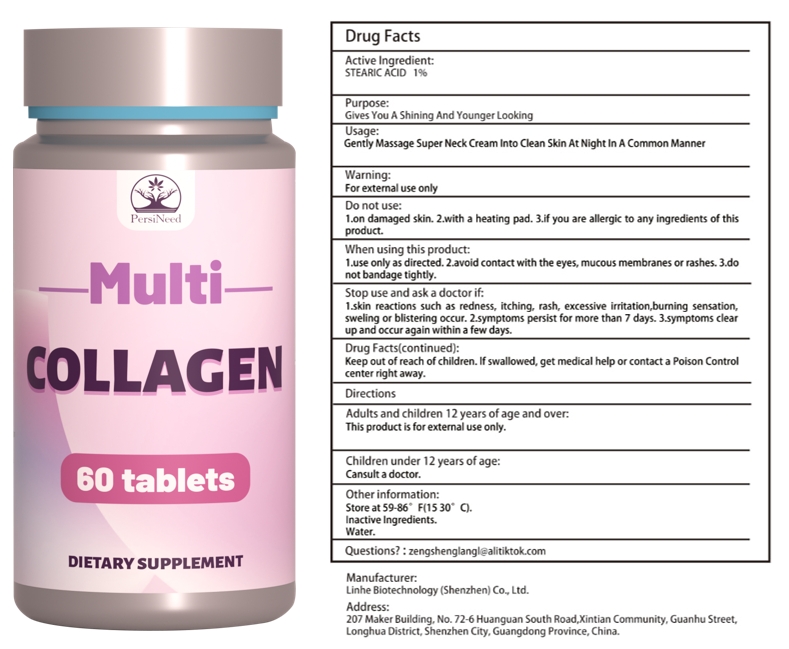 DRUG LABEL: Multi COLLAGEN
NDC: 84575-067 | Form: CAPSULE
Manufacturer: Linhe Biotechnology (Shenzhen) Co., Ltd
Category: otc | Type: HUMAN OTC DRUG LABEL
Date: 20241127

ACTIVE INGREDIENTS: COLLAGEN, SOLUBLE, FISH SKIN 0.6 g/60 g
INACTIVE INGREDIENTS: CINNAMON

Collagen

ACTIVE INGREDIENT

Collagen 1%

PURPOSE

Dietary Supplement

INDICATIONS AND USAGE

Preferably with a meal and water, or as directed by a health care professional.

WARNINGS

Minors, pregnant women, and breastfeeding mothers are not allowed to consume.This product is notintended to diagnose,treat, cure or prevent any disease.

DOSAGE AND ADMINISTRATION

Contains no wheat, eggs, artificial colours, flavours or preservatives.As a dietary supplement, take 2 capsules once per day.

INACTIVE INGREDIENT

CINNAMON

STORAGE AND HANDLING

Store in a cool and dark place away from light

Keep out of reach of children,in case of overdose, get medical help or contact a PoisonControl Center right away.